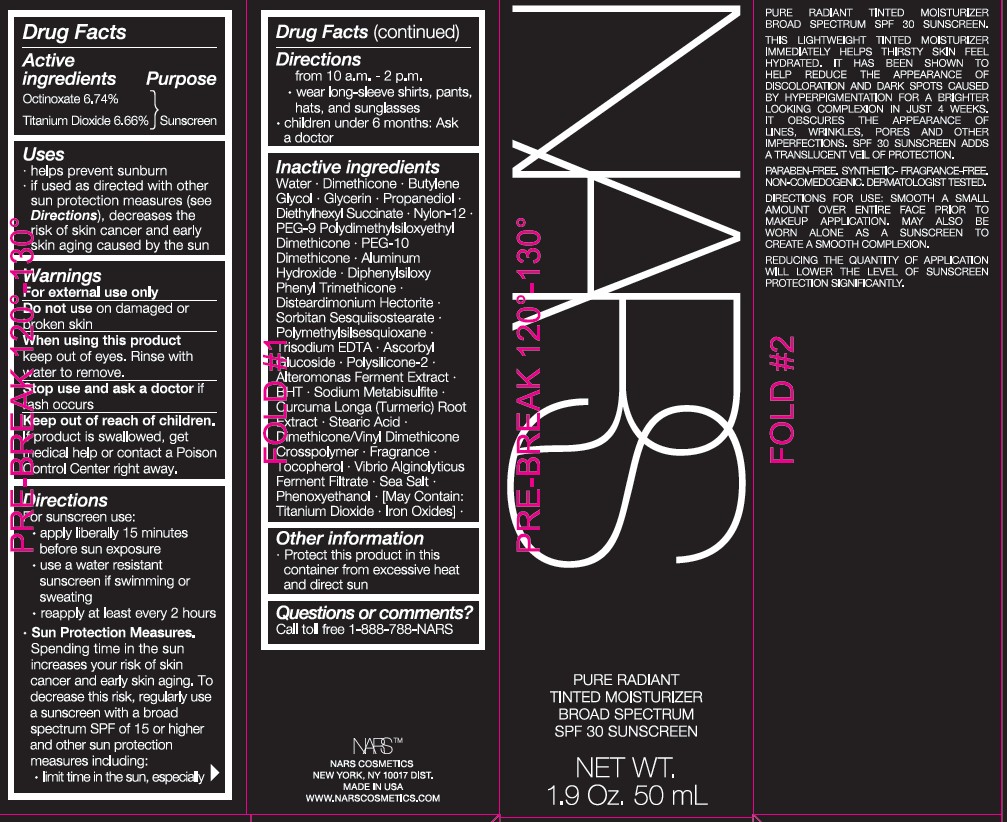 DRUG LABEL: NARS PURE RADIANT TINTED MOISTURIZER

NDC: 13734-177 | Form: CREAM
Manufacturer: NARS Cosmetics
Category: otc | Type: HUMAN OTC DRUG LABEL
Date: 20251218

ACTIVE INGREDIENTS: OCTINOXATE 4.044 g/50 mL; TITANIUM DIOXIDE 3.996 g/50 mL
INACTIVE INGREDIENTS: WATER; DIMETHICONE; BUTYLENE GLYCOL; GLYCERIN; PROPANEDIOL; DIETHYLHEXYL SUCCINATE; NYLON-12; PEG-9 POLYDIMETHYLSILOXYETHYL DIMETHICONE; PEG-10 DIMETHICONE (200 CST); ALUMINUM HYDROXIDE; DIPHENYLSILOXY PHENYL TRIMETHICONE; DISTEARDIMONIUM HECTORITE; SORBITAN SESQUIISOSTEARATE; POLYMETHYLSILSESQUIOXANE (11 MICRONS); TRISODIUM EDTA; ASCORBYL GLUCOSIDE; ALTEROMONAS MACLEODII; BHT; SODIUM METABISULFITE; TOCOPHEROL; CURCUMA LONGA (TURMERIC) ROOT; STEARIC ACID; DIMETHICONE/VINYL DIMETHICONE CROSSPOLYMER (HARD PARTICLE); SEA SALT; PHENOXYETHANOL; FERRIC OXIDE RED

NARS PURE RADIANT TINTED MOISTURIZER

Drug Facts

Active Ingredients | Purpose
Octinoxate 6.74% | Sunscreen
Titanium Dioxide 6.66% | Sunscreen

Uses

- helps prevent sunbun
- if used as directed with other sun protection measures (see Directions), decreases the risk of skin cancer and early skin aging caused by the sun

Warnings

For external use only

Do not useon damaged or broken skin

WHEN USING

When using this productkeep out of eyes. Rinse with water to remove.

Stop use and ask a doctorif rash occurs

Keep out of reach of children.If product is swallowed, get medical help or contact a Poison Control Center right away.

Directions

For sunscreen use:

- apply liberally 15 minutes before sun exposure
- use a water resistant sunscreen if swimming or sweating
- reapply at least every 2 hours
- Sun Protection Measures.Spending time in the sun increases your risk of skin cancer and early skin aging. To decrease this risk, regularly use a sunscreen with a broad spectrum SPF of 15 or higher and other sun protection mesures including:

• limit time in the sun, especially from 10 a.m. - 2 p.m.
• wear long-sleeve shirts, pants, hats, and sunglasses

- children under 6 months: Ask a doctor

INACTIVE INGREDIENT

WATER • DIMETHICONE • BUTYLENE GLYCOL • GLYCERIN • PROPANEDIOL • DIETHYLHEXYL SUCCINATE • NYLON-12 • PEG-9 POLYDIMETHYLSILOXYETHYL DIMETHICONE • PEG-10 DIMETHICONE • ALUMINUM HYDROXIDE • DIPHENYLSILOXY PHENYL TRIMETHICONE • DISTEARDIMONIUM HECTORITE • SORBITAN SESQUIISOSTEARATE • POLYMETHYLSILSESQUIOXANE • TRISODIUM EDTA • ASCORBYL GLUCOSIDE • POLYSILICONE-2 • ALTEROMONAS FERMENT EXTRACT • BHT • SODIUM METABISULFITE • CURCUMA LONGA (TURMERIC) ROOT EXTRACT • STEARIC ACID • DIMETHICONE/VINYL DIMETHICONE CROSSPOLYMER • FRAGRANCE • TOCOPHEROL • VIBRIO ALGINOLYTICUS FERMENT FILTRATE • SEA SALT • PHENOXYETHANOL • [MAY CONTAIN: TITANIUM DIOXIDE • IRON OXIDES] •

Other information

- Protect this product in this container from excessive heat and direct sun

Questions or comments?

- Call toll free 1-888-788-NARS

PRINCIPLE DISPLAY PANEL - 50 mL Tube Cuzco

NARS

PURE RADIANT

TINTED MOISTURIZER

BROAD SPECTRUM

SPF 30 SUNSCREEN

NET WT. 1.9 Oz. 50 mL

PRINCIPLE DISPLAY PANEL - 50 mL Tube St. Moritz

NARS

PURE RADIANT

TINTED MOISTURIZER

BROAD SPECTRUM

SPF 30 SUNSCREEN

NET WT. 1.9 Oz. 50 mL

PRINCIPLE DISPLAY PANEL - 50 mL Tube Groenland

NARS

PURE RADIANT

TINTED MOISTURIZER

BROAD SPECTRUM

SPF 30 SUNSCREEN

NET WT. 1.9 Oz. 50 mL

PRINCIPLE DISPLAY PANEL - 50 mL Tube Alaska

NARS

PURE RADIANT

TINTED MOISTURIZER

BROAD SPECTRUM

SPF 30 SUNSCREEN

NET WT. 1.9 Oz. 50 mL

PRINCIPLE DISPLAY PANEL - 50 mL Tube Finland

NARS

PURE RADIANT

TINTED MOISTURIZER

BROAD SPECTRUM

SPF 30 SUNSCREEN

NET WT. 1.9 Oz. 50 mL

PRINCIPLE DISPLAY PANEL - 50 mL Tube Terre Neuve

NARS

PURE RADIANT

TINTED MOISTURIZER

BROAD SPECTRUM

SPF 30 SUNSCREEN

NET WT. 1.9 Oz. 50 mL

PRINCIPLE DISPLAY PANEL - 50 mL Tube Gotland

NARS

PURE RADIANT

TINTED MOISTURIZER

BROAD SPECTRUM

SPF 30 SUNSCREEN

NET WT. 1.9 Oz. 50 mL

PRINCIPLE DISPLAY PANEL - 50 mL Tube Norwich

NARS

PURE RADIANT

TINTED MOISTURIZER

BROAD SPECTRUM

SPF 30 SUNSCREEN

NET WT. 1.9 oz. 50 mL

PRINCIPLE DISPLAY PANEL - 50 mL Tube Mykonos

NARS

PURE RADIANT

TINTED MOISTURIZER

BROAD SPECTRUM

SPF 30 SUNSCREEN

NET WT. 1.9 Oz. 50 mL

PRINCIPLE DISPLAY PANEL - 50 mL Tube Sydney

NARS

PURE RADIANT

TINTED MOISTURIZER

BROAD SPECTRUM

SPF 30 SUNSCREEN

NET WT. 1.9 Oz. 50 mL

PRINCIPLE DISPLAY PANEL - 50 mL Tube Auckland

NARS

PURE RADIANT

TINTED MOISTURIZER

BROAD SPECTRUM

SPF 30 SUNSCREEN

NET WT. 1.9 Oz. 50 mL

PRINCIPLE DISPLAY PANEL - 50 mL Tube Marrakesh

NARS

PURE RADIANT

TINTED MOISTURIZER

BROAD SPECTRUM

SPF 30 SUNSCREEN

NET WT. 1.9 Oz. 50 mL

PRINCIPLE DISPLAY PANEL - 50 mL Tube Santiago

NARS

PURE RADIANT

TINTED MOISTURIZER

BROAD SPECTRUM

SPF 30 SUNSCREEN

NET WT. 1.9 Oz. 50 mL

PRINCIPLE DISPLAY PANEL - 50 mL Tube Havana

NARS

PURE RADIANT

TINTED MOISTURIZER

BROAD SPECTRUM

SPF 30 SUNSCREEN

NET WT. 1.9 Oz. 50 mL

PRINCIPLE DISPLAY PANEL - 50 mL Tube Guernsey

NARS

PURE RADIANT

TINTED MOISTURIZER

BROAD SPECTRUM

SPF 30 SUNSCREEN

NET WT. 1.9 Oz. 50 mL

PRINCIPLE DISPLAY PANEL - 50 mL Tube Granada

NARS

PURE RADIANT

TINTED MOISTURIZER

BROAD SPECTRUM

SPF 30 SUNSCREEN

NET WT. 1.9 Oz. 50 mL